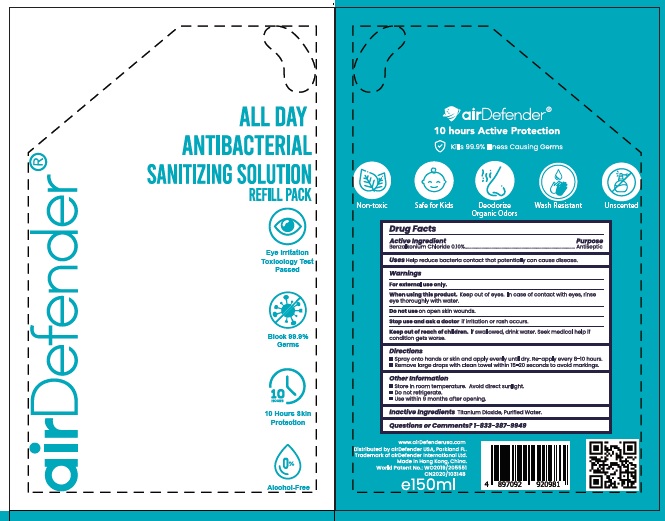 DRUG LABEL: airDefender All Day Antibacterial Sanitizing Solution Refill Pack
NDC: 78976-003 | Form: SOLUTION
Manufacturer: Airdefender International Company Limited
Category: otc | Type: HUMAN OTC DRUG LABEL
Date: 20210127

ACTIVE INGREDIENTS: BENZALKONIUM CHLORIDE 1 mg/1 mL
INACTIVE INGREDIENTS: WATER; TITANIUM DIOXIDE

airDefender All Day Antibacterial Sanitizing Solution Refill Pack (78976-003-25)

Active Ingredient(s)

Benzalkonium Chloride 0.10%

Purpose

Antiseptic

Use

Help reduce bacteria contact that potentially can cause disease.

Warnings

For external use only.

Do not use

- on open skin wounds

WHEN USING

Keep out of eyes. In case of contact with eyes, rinse eye thoroughly with water.

Stop use and ask a doctor if irritation or rash occurs.

KEEP OUT OF REACH OF CHILDREN

If swallowed, drink water. Seek medical help if condition gets worse.

Directions

- Spray onto hands or skin and apply evenly until dry.
- Remove large drops with clean towel within 15-20 seconds to avoid markings

Other information

- Store in room temperature. Avoid direct sunlight.
- Do not refrigerate.
- Use within 9 months after opening

Inactive ingredients

Titanium Dioxide, Purified Water

Questions or Comments?

1-833-387-9949